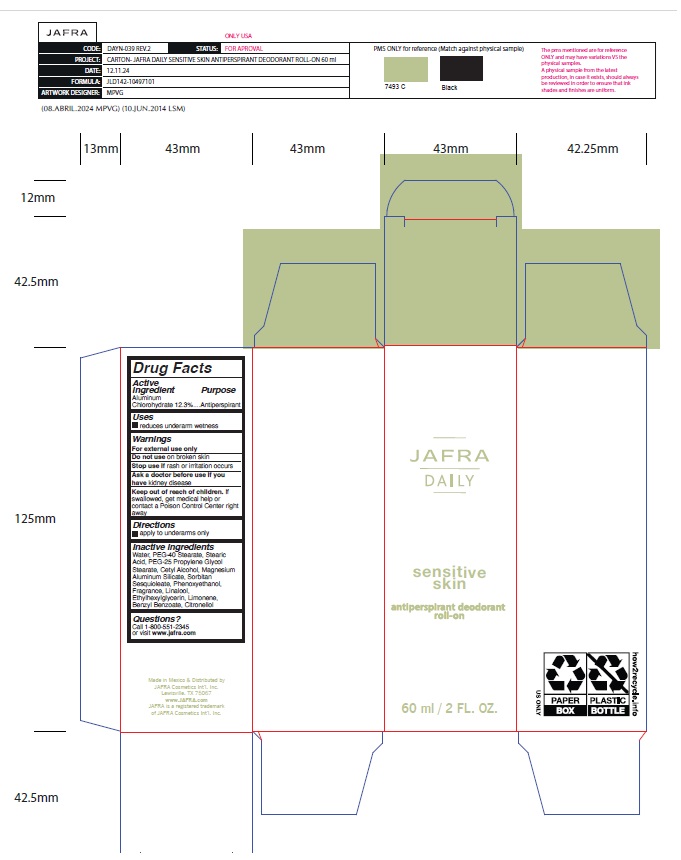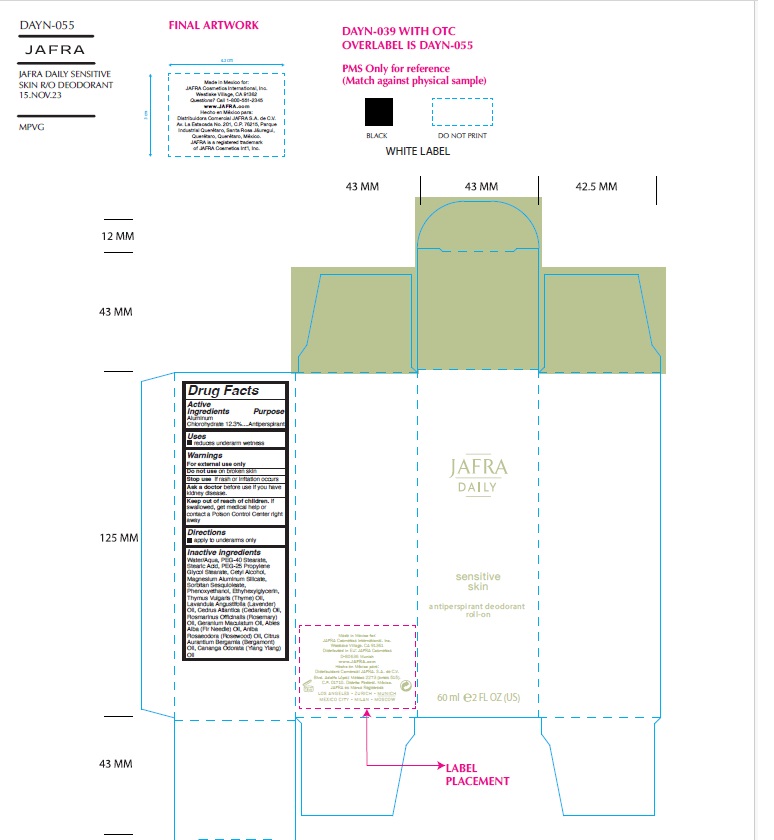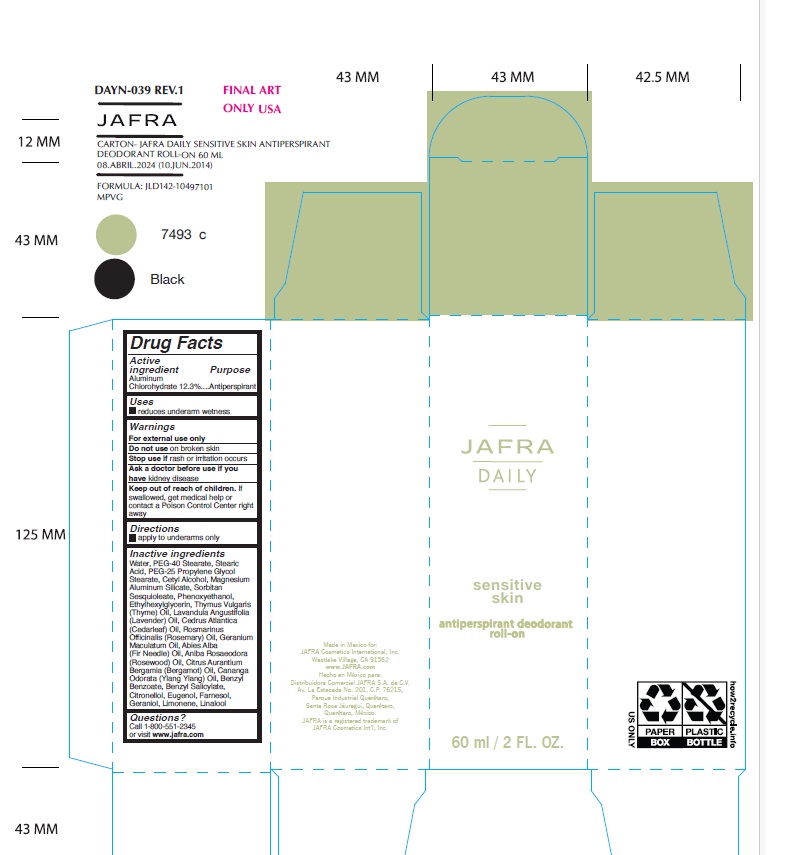 DRUG LABEL: Jafra Daily Sensitive Skin Antiperspirant Deodorant Roll-on
NDC: 68828-705 | Form: LIQUID
Manufacturer: Distribuidora Comercial Jafra, S.A. de C.V.
Category: otc | Type: HUMAN OTC DRUG LABEL
Date: 20250102

ACTIVE INGREDIENTS: ALUMINUM CHLOROHYDRATE 12.3 g/100 mL
INACTIVE INGREDIENTS: WATER; PEG-40 MONOSTEARATE; PEG-25 PROPYLENE GLYCOL STEARATE; SORBITAN SESQUIOLEATE; CETYL ALCOHOL; MAGNESIUM ALUMINUM SILICATE; PHENOXYETHANOL; ETHYLHEXYLGLYCERIN; LINALOOL, (+/-)-; BENZYL BENZOATE; .BETA.-CITRONELLOL, (+/-)-; STEARIC ACID; LIMONENE, (+)-

Jafra Daily Sensitive Skin Antiperspirant Deodorant Roll-on

Active ingredient

Aluminum Chlorohydrate 12.3 %

Purpose

Antiperspirant

Uses

- Reduces underarm wetness

Warnings

For external use only
Do not use on broken skin
Stop use ifrash or irritation occurs
Ask a doctor before use if you havekidney disease

Keep out of reach of children.If swallowed, get medical help or contact a Poison Control Center right away.

Directions

- Apply to underarms only

Inactive Ingredients

Water, PEG-40 Stearate, Stearic Acid, PEG-25 Propylene Glycol Stearate, Cetyl Alcohol, Magnesium Aluminum Silicate, Sorbitan Sesquioleate, Phenoxyethanol, Fragrance, Linalool, Ethylhexylglycerin, Limonene, Benzyl Benzoate, Citronellol

Questions?Call 1-800-551-2345 or visit www.jafra.com